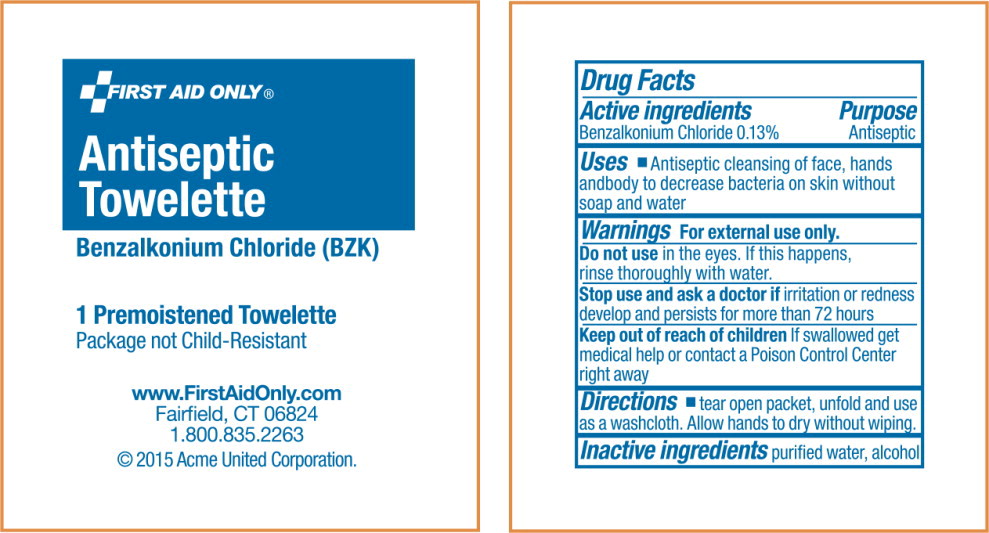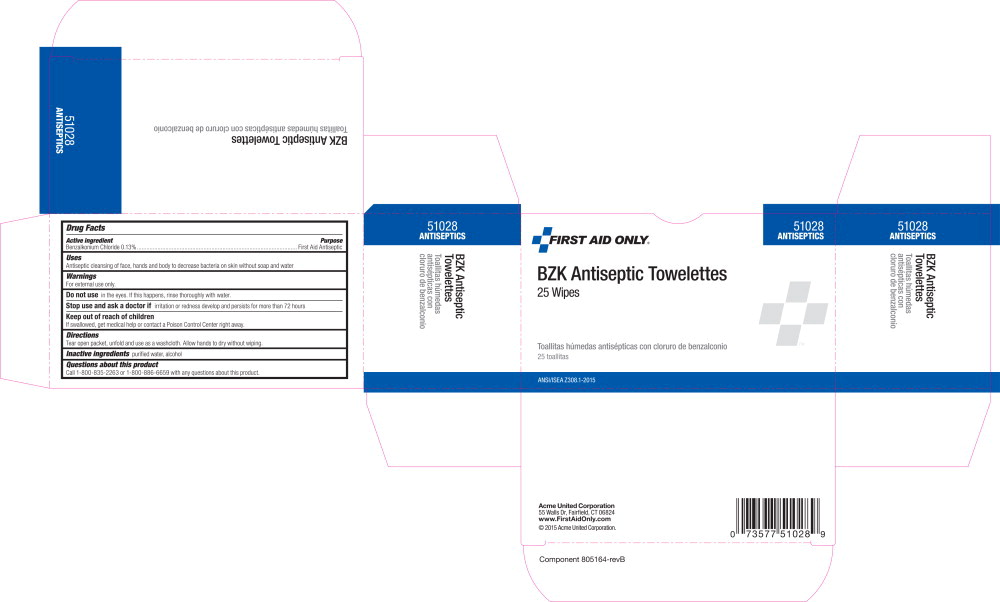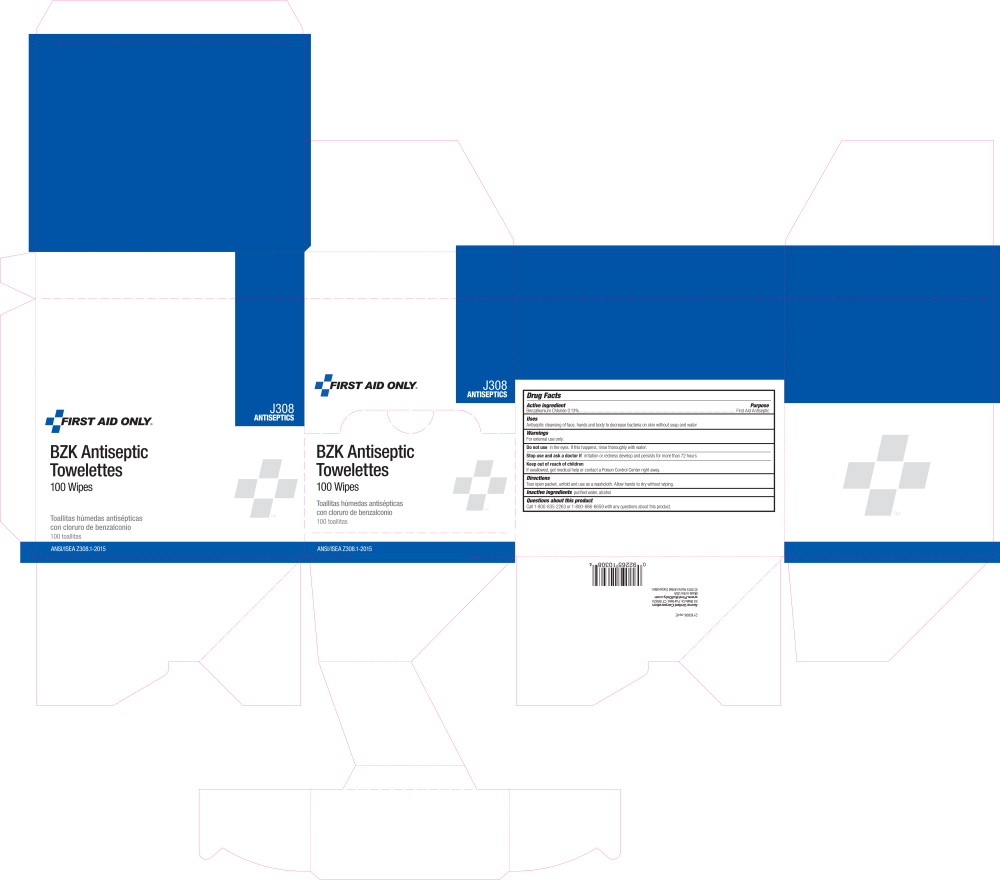 DRUG LABEL: Antiseptic
NDC: 0924-7110 | Form: LIQUID
Manufacturer: Acme United Corporation
Category: otc | Type: HUMAN OTC DRUG LABEL
Date: 20151120

ACTIVE INGREDIENTS: benzalkonium chloride 1.2478 g/1 L
INACTIVE INGREDIENTS: alcohol; water

Drug Facts

Active Ingredients

Benzalkonium Chloride 0.13%

Purpose

Antiseptic

Uses

- Antiseptic cleansing of face, hands and body to decrease bacteria on skin without soap and water

Warnings

For external use only

Do not use in the eyes. If this happens, rinse thoroughly with water.

Stop use and ask doctor if irritation or redness develop and persists for more than 72 hours

Keep out of reach of children If swallowed, get medical help or contact a Poison Control Center right away

Directions

- tear open packet, unfold and use as a washcloth. Allow hands to dry without wiping.

Inactive ingredients

Purified water, alcohol

Principal Display Panel - Packet Label

FIRST AID ONLY®

Antiseptic
Towelette

Benzalkonium Chloride (BZK)

1 Premoistened Towelette

Package not Child-Resistant

www.FirstAidOnly.com

Fairfield, CT 06824

1.800.835.2263

© 2015 Acme United Corporation.

Principal Display Panel - Box Label

FIRST AID ONLY®

51028

ANTISEPTICS

BZK Antiseptic Towelettes

25 Wipes

Toallitas húmedas antisépticas con cloruro de benzalconio

25 toallitas

Principal Display Panel - Box Label

J308
ANTISEPTICS

First Aid Only®

BZK Antiseptic
Towlettes

100 Wipes

Toallitas húmedas antisépticas
con cloruro de benzalconio

100 toallitas